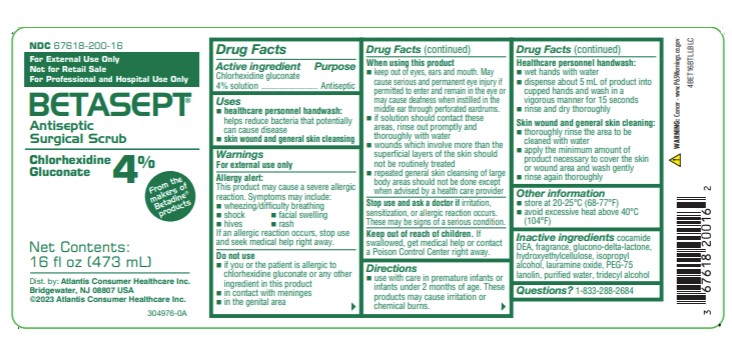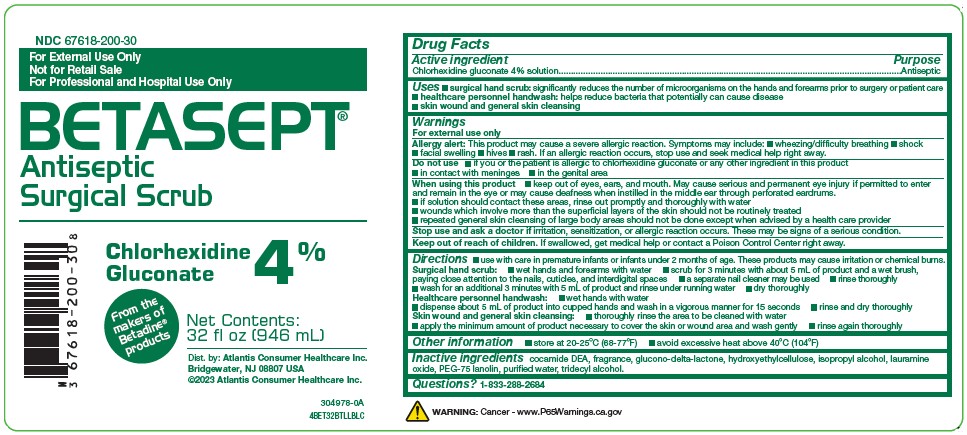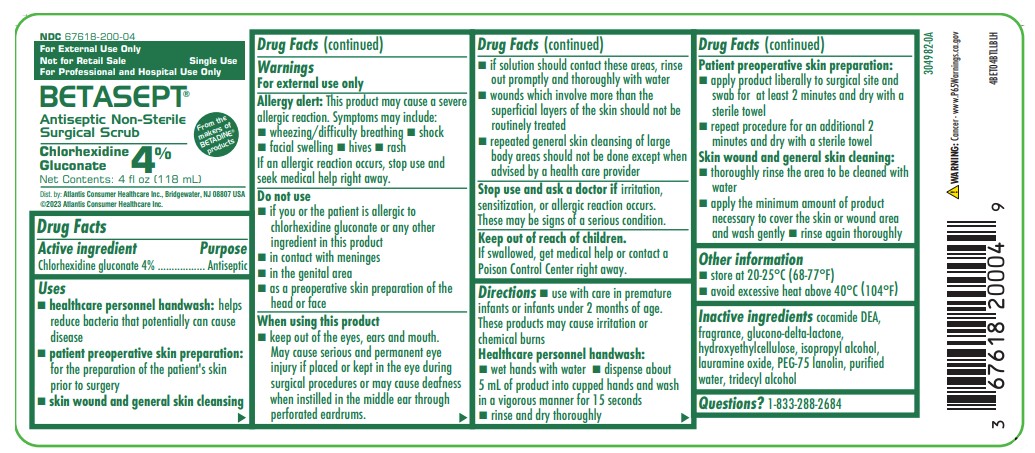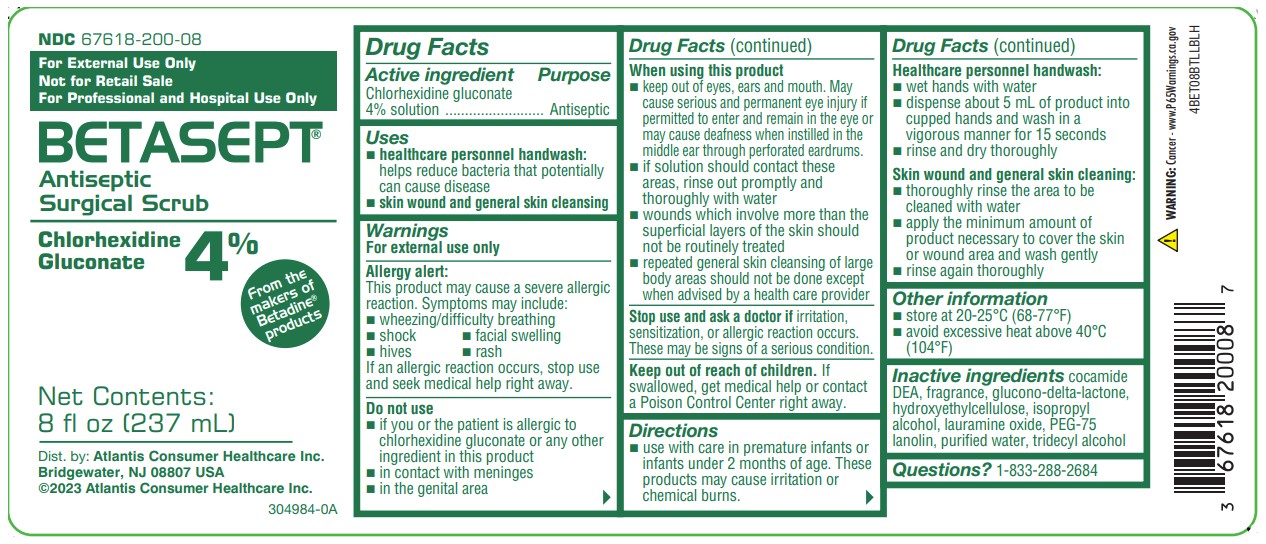 DRUG LABEL: BETASEPT
NDC: 0116-0200 | Form: SOLUTION
Manufacturer: Xttrium Laboratories, Inc.
Category: prescription | Type: HUMAN PRESCRIPTION DRUG LABEL
Date: 20250430

ACTIVE INGREDIENTS: CHLORHEXIDINE GLUCONATE 0.04 mg/1 mL
INACTIVE INGREDIENTS: GLUCONOLACTONE; ISOPROPYL ALCOHOL; LAURAMINE OXIDE; PEG-75 LANOLIN; WATER; TRIDECYL ALCOHOL; COCO DIETHANOLAMIDE

XTT BETASEPT Antiseptic Surgical Scrub
Chlorhexidine Gluconate 4%

Active ingredient

Chlorhexidine gluconate 4% solution

Purpose

Antiseptic

Uses

- surgical hand scrub: significantly reduces the number of microorganisms on the hands and forearms prior to surgery or patient care
- healthcare personnel handwash: helps reduce bacteria that potentially can cause disease
- patient preoperative skin preparation: preparation of the patient's skin prior to surgery
- skin wound and general skin cleansing

Warnings

For external use only

Allergy alert:

This product may cause a severe allergic reaction. Symptoms may include:

- wheezing/difficulty breathing
- shock
- facial swelling
- hives
- rash

If an allergic reaction, stop use and seek medical help right away.

Do not use

- if you or the patient is allergic to chlorhexidine gluconate or any other ingredient in this product
- in contact with meninges
- in the genital area
- as a preoperative skin preparation of the head or face

When using this product

- keep out of the eyes, ears, and mouth. May cause serious and permanent eye injury if placed or kept in the eye during surgical procedures or may cause deafness when instilled in the middle ear through perforated eardrums.
- if solution should contact these areas, rinse out promptly and thoroughly with water
- wounds which involve more than the superficial layers of the skin should not be routinely treated
- repeated general skin cleansing of large body areas should not be done except when advised by a health care provider

Stop use and ask a doctor if

irritation, sensitization, or allergic reaction occurs. These may be signs of a serious condition.

Keep out of reach of children.

If swallowed, get medical help or contact a Poison Control Center right away.

Directions

- use with care in premature infants or infants under 2 months of age. These products may cause irritation or chemical burns.

Surgical hand scrub

- wet hands and forearms with water
- scrub for 3 minutes with about 5 mL of product and a wet brush, paying close attention to the nails, cuticles, and interdigital spaces
- a seperate nail cleaner may be used
- rinse thoroughly
- wash for an additional 3 minutes with 5 mL of product and rinse under running water
- dry thoroughly

Healthcare personnel handwash

- wet hands with water
- dispense about 5 mL of priduct into cupped hands and wash in a vigorous manner for 15 seconds
- rinse and dry thoroughly

Patient preoperative skin preparation

- apply product liberally to surgical site and swab for at least 2 minutes and dry with a sterile towel
- repeat procedure for an additional 2 minutes and dry with a sterile towel

Skin wound and general skin cleansing

- thoroughly rinse the area to be cleaned with water
- apply the minimum amount of product necessary to cover the skin or wound area and wash gently
- rinse again thoroughly

Other information

store at 20-25°C (68-77°F)

avoid excessive heat above 40°C (104°F)

Inactive ingredients

cocamide DEA, fragrance, glucono-delta-lactone, hydroxyethylcellulose, isopropyl alcohol, lauramine oxide, PEG-75 lanolin, purified water, tridecyl alcohol

Questions or comments?

call 1-888-827-0624 (8am-5pm, EST, Mon-Fri)

OTHER SAFETY INFORMATION

WARNING: Cancer - www.P65Warnings.ca.gov

PACKAGE LABEL

NDC 67618-200-04

From the Makers of BETADINE® products

For External Use Only

Not for Retail Sale

For Professional and Hospital Use Only

Single Use

BETASEPT®

Antiseptic Non-Sterile Surgical Scrub

Chlorhexidine Gluconate 4%

Net Contents: 4 fl oz (118 mL)

Dist. by: Atlantis Consumer Healthcare Inc. Bridgewater, NJ 08807 USA

©2023 Atlantis Consumer Healthcare Inc.

4BET04BTLLBLH

NDC 67618-200-08

From the Makers of BETADINE® products

For External Use Only

Not for Retail Sale

For Professional and Hospital Use Only

BETASEPT®

Antiseptic Surgical Scrub

Chlorhexidine Gluconate 4%

Net Contents: 8 fl oz (237 mL)

Dist. by:Atlantis Consumer Healthcare Inc. Bridgewater, NJ 08807 USA

©2023 Atlantis Consumer Healthcare Inc.

4BET08BTLLBLH

NDC 67618-200-16

From the Makers of BETADINE® products

For External Use Only

Not for Retail Sale

For Professional and Hospital Use Only

BETASEPT®

Antiseptic Surgical Scrub

Chlorhexidine Gluconate 4%

Net Contents: 16 fl oz (473 mL)

Dist. by: Atlantis Consumer Healthcare Inc. Bridgewater, NJ 08807 USA

©2023 Atlantis Consumer Healthcare Inc.

4BET16BTLLBLC

NDC 67618-200-32

From the Makers of BETADINE® products

For External Use Only

Not for Retail Sale

For Professional and Hospital Use Only

BETASEPT®

Antiseptic Surgical Scrub

Chlorhexidine Gluconate 4%

Net Contents: 32 fl oz (946 mL)

Dist. by: Atlantis Consumer Healthcare Inc. Bridgewater, NJ 08807 USA

©2023 Atlantis Consumer Healthcare Inc.

4BET32PBTLLBLC